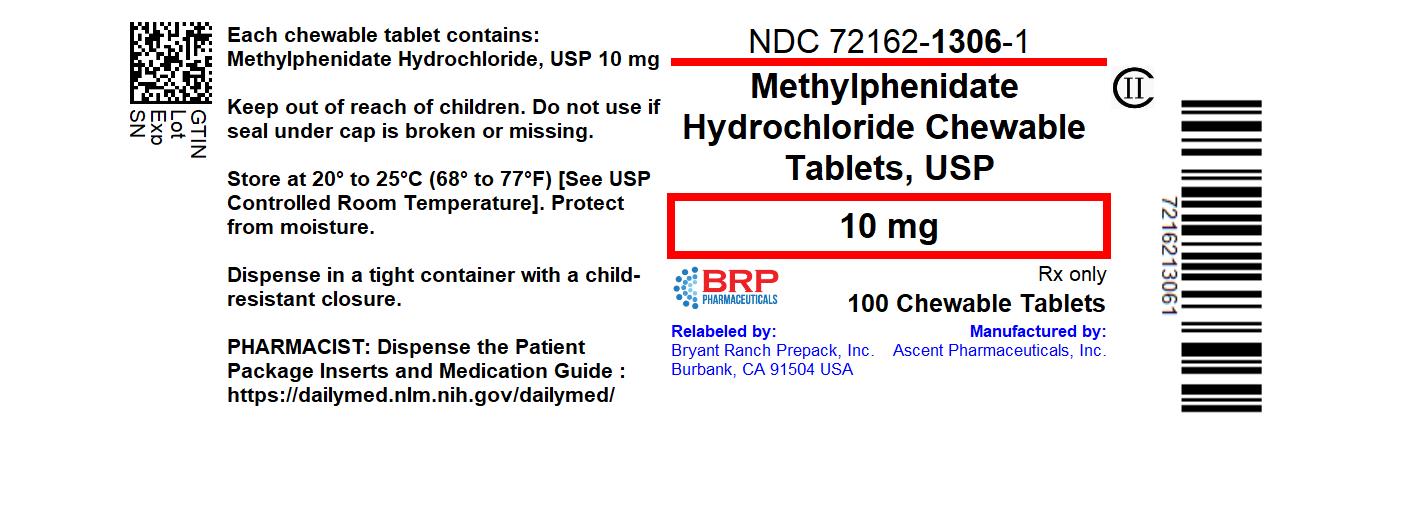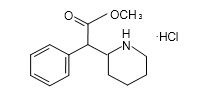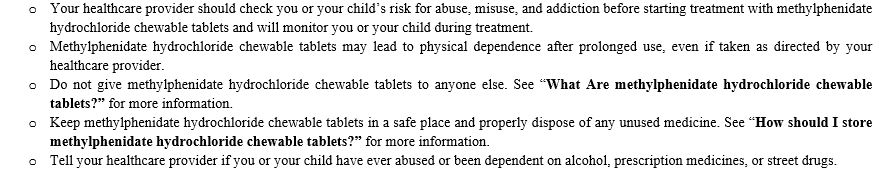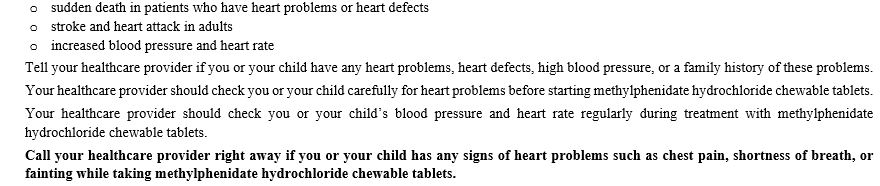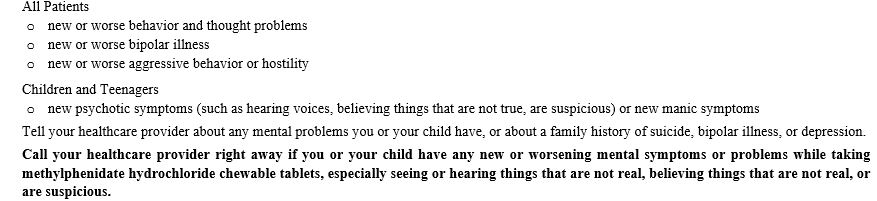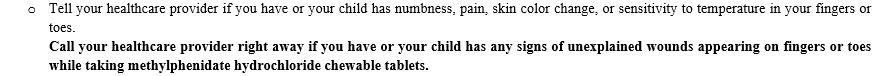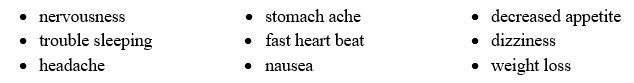 DRUG LABEL: Methylphenidate Hydrochloride
NDC: 72162-1306 | Form: TABLET, CHEWABLE
Manufacturer: Bryant Ranch Prepack
Category: prescription | Type: HUMAN PRESCRIPTION DRUG LABEL
Date: 20240205
DEA Schedule: CII

ACTIVE INGREDIENTS: METHYLPHENIDATE HYDROCHLORIDE 10 mg/1 1
INACTIVE INGREDIENTS: ASPARTAME; ANHYDROUS LACTOSE; MICROCRYSTALLINE CELLULOSE; GUAR GUM; STARCH, CORN; STEARIC ACID

Methylphenidate HCl Chewable Tablet, CII
Rx only

WARNING: ABUSE, MISUSE, AND ADDICTION

Methylphenidate hydrochloride chewable tablets has a high potential for abuse and misuse, which can lead to the development of a substance use disorder, including addiction. Misuse and abuse of CNS stimulants, including methylphenidate hydrochloride chewable tablets, can result in overdose and death ([see Overdosage]), and this risk is increased with higher doses or unapproved methods of administration, such as snorting or injection.

Before prescribing methylphenidate hydrochloride chewable tablets, assess each patient’s risk for abuse, misuse, and addiction. Educate patients and their families about these risks, proper storage of the drug, and proper disposal of any unused drug. Throughout methylphenidate hydrochloride chewable tablets treatment, reassess each patient’s risk of abuse, misuse, and addiction and frequently monitor for signs and symptoms of abuse, misuse, and addiction (see Warnings and Precautions and Drug Abuse and Dependence).

DESCRIPTION

Methylphenidate hydrochloride chewable tablets are a mild central nervous system (CNS) stimulant, available as 2.5 mg, 5 mg and 10 mg for oral administration. Methylphenidate hydrochloride is methyl α-phenyl-2-piperidineacetate hydrochloride, and its structural formula is

Methylphenidate Hydrochloride

C14H19NO2• HCl MW = 269.77

Methylphenidate hydrochloride USP is a white, odorless, fine crystalline powder. Its solutions are acid to litmus. It is freely soluble in water and in methanol, soluble in alcohol, and slightly soluble in chloroform and in acetone.

Each methylphenidate hydrochloride chewable tablet, for oral administration, contains 2.5 mg, 5 mg or 10 mg of methylphenidate hydrochloride USP. In addition, methylphenidate hydrochloride chewable tablets also contain the following inactive ingredients: aspartame, lactose anhydrous, microcrystalline cellulose, guar gum, grape flavor, pregelatinized starch, and stearic acid.

CLINICAL PHARMACOLOGY

Methylphenidate is a racemic mixture comprised of the d- and l-threo enantiomers. The d-threo enantiomer is more pharmacologically active than the l-threo enantiomer.

Methylphenidate HCl is a central nervous system (CNS) stimulant.

The mode of therapeutic action in humans is not completely understood, but methylphenidate presumably activates the brain stem arousal system and cortex to produce its stimulant effect. Methylphenidate is thought to block the reuptake of norepinephrine and dopamine into the presynaptic neuron and increase the release of these monoamines into the extraneuronal space.

There is neither specific evidence which clearly establishes the mechanism whereby methylphenidate hydrochloride chewable tablets produces its mental and behavioral effects in children, nor conclusive evidence regarding how these effects relate to the condition of the central nervous system.

Pharmacokinetics
Absorption
Methylphenidate hydrochloride chewable tablets are readily absorbed. Following oral administration of methylphenidate hydrochloride chewable tablets, peak plasma methylphenidate concentrations are achieved at about 1 to 2 hours. Methylphenidate hydrochloride chewable tablets have been shown to be bioequivalent to Ritalin® tablet. The mean Cmax following a 20 mg dose is approximately 10 ng/mL.

Food Effect
In a study in adult volunteers investigating the effects of a high-fat meal on the bioavailability of methylphenidate hydrochloride chewable tablets at a dose of 20 mg, the presence of food delayed the peak concentrations by approximately 1 hour (1.5 hours, fasted and 2.4 hours, fed). Overall, a high-fat meal increased the AUC of methylphenidate hydrochloride chewable tablets by about 20%, on average. Through a cross-study comparison, the magnitude of food effect is found to be comparable between the methylphenidate hydrochloride chewable tablets and Ritalin, the immediate release tablet.

Metabolism and Excretion
In humans, methylphenidate is metabolized primarily via deesterification to alpha-phenylpiperidine acetic acid (PPA, ritalinic acid). The metabolite has little or no pharmacologic activity.

After oral dosing of radiolabeled methylphenidate in humans, about 90% of the radioactivity was recovered in urine. The main urinary metabolite was PPA, accounting for approximately 80% of the dose.

The pharmacokinetics of the methylphenidate hydrochloride chewable tablets have been studied in healthy adult volunteers. The mean terminal half-life (t½) of methylphenidate following administration of 20 mg methylphenidate hydrochloride chewable tablets (t½ = 3 hours) is comparable to the mean terminal t½ following administration of Ritalin (methylphenidate hydrochloride immediate-release tablets) (t½ = 2.8 hours) in healthy adult volunteers.

Special Populations
Gender – The effect of gender on the pharmacokinetics of methylphenidate after methylphenidate hydrochloride chewable tablets administration has not been studied.

Race – The influence of race on the pharmacokinetics of methylphenidate after methylphenidate hydrochloride chewable tablets administration has not been studied.

Age – The pharmacokinetics of methylphenidate after methylphenidate hydrochloride chewable tablets administration have not been studied in pediatrics.

Renal Insufficiency
There is no experience with the use of methylphenidate hydrochloride chewable tablets in patients with renal insufficiency. After oral administration of radiolabeled methylphenidate in humans, methylphenidate was extensively metabolized and approximately 80% of the radioactivity was excreted in the urine in the form of ritalinic acid. Since renal clearance is not an important route of methylphenidate clearance, renal insufficiency is expected to have little effect on the pharmacokinetics of methylphenidate hydrochloride chewable tablets.

Hepatic Insufficiency
There is no experience with the use of methylphenidate hydrochloride chewable tablets in patients with hepatic insufficiency.

INDICATIONS AND USAGE

Attention Deficit Disorders, Narcolepsy
Attention Deficit Disorders (previously known as Minimal Brain Dysfunction in Children). Other terms being used to describe the behavioral syndrome below include: Hyperkinetic Child Syndrome, Minimal Brain Damage, Minimal Cerebral Dysfunction, Minor Cerebral Dysfunction.

Methylphenidate hydrochloride chewable tablets are indicated as an integral part of a total treatment program which typically includes other remedial measures (psychological, educational, social) for a stabilizing effect in children with a behavioral syndrome characterized by the following group of developmentally inappropriate symptoms: moderate-to-severe distractibility, short attention span, hyperactivity, emotional lability, and impulsivity. The diagnosis of this syndrome should not be made with finality when these symptoms are only of comparatively recent origin. Nonlocalizing (soft) neurological signs, learning disability, and abnormal EEG may or may not be present, and a diagnosis of central nervous system dysfunction may or may not be warranted.

Special Diagnostic Considerations
Specific etiology of this syndrome is unknown, and there is no single diagnostic test. Adequate diagnosis requires the use not only of medical but of special psychological, educational, and social resources.

Characteristics commonly reported include: chronic history of short attention span, distractibility, emotional lability, impulsivity, and moderate-to-severe hyperactivity; minor neurological signs and abnormal EEG. Learning may or may not be impaired. The diagnosis must be based upon a complete history and evaluation of the child and not solely on the presence of one or more of these characteristics.

Drug treatment is not indicated for all children with this syndrome. Stimulants are not intended for use in the child who exhibits symptoms secondary to environmental factors and/or primary psychiatric disorders, including psychosis. Appropriate educational placement is essential and psychosocial intervention is generally necessary. When remedial measures alone are insufficient, the decision to prescribe stimulant medication will depend upon the physician’s assessment of the chronicity and severity of the child’s symptoms.

CONTRAINDICATIONS

Methylphenidate hydrochloride chewable tablets are contraindicated in patients known to be hypersensitive to methylphenidate or other components of the drug.

Methylphenidate hydrochloride chewable tablets are contraindicated during treatment with monoamine oxidase inhibitors, and also within a minimum of 14 days following discontinuation of a monoamine oxidase inhibitor (hypertensive crises may result).

WARNINGS

Abuse, Misuse, and Addiction
Methylphenidate hydrochloride chewable tablets has a high potential for abuse and misuse. The use of methylphenidate hydrochloride chewable tablets exposes individuals to the risks of abuse and misuse, which can lead to the development of a substance use disorder, including addiction. Methylphenidate hydrochloride chewable tablets can be diverted for non-medical use into illicit channels or distribution (see DRUG ABUSE and DEPENDENCE). Misuse and abuse of CNS stimulants, including methylphenidate hydrochloride chewable tablets can result in overdose and death (see OVERDOSAGE), and this risk is increased with higher doses or unapproved methods of administration, such as snorting or injection.

Before prescribing methylphenidate hydrochloride chewable tablets, assess each patient’s risk for abuse, misuse, and addiction. Educate patients and their families about these risks and proper disposal of any unused drug. Advise patients to store methylphenidate in a safe place, preferably locked, and instruct patients to not give methylphenidate hydrochloride chewable tablets to anyone else. Throughout methylphenidate hydrochloride chewable tablets treatment, reassess each patient’s risk of abuse, misuse, and addiction and frequently monitor for signs and symptoms of abuse, misuse, and addiction.

Risks to Patients with Serious Cardiac Disease
Sudden death has been reported in patients with structural cardiac abnormalities or other serious cardiac disease who are treated with CNS stimulants at the recommended ADHD dosages.

Avoid methylphenidate hydrochloride chewable tablets use in patients with known structural cardiac abnormalities, cardiomyopathy, serious cardiac arrhythmia, coronary artery disease, or other serious cardiac disease.

Increased Blood Pressure and Heart Rate
CNS stimulants cause an increase in blood pressure (mean increase about 2 to 4 mm Hg) and heart rate (mean increase about 3 to 6 bpm). Monitor all patients for potential tachycardia and hypertension.

Psychiatric Adverse Reactions
Exacerbations of Pre-Existing Psychosis – CNS stimulants may exacerbate symptoms of behavior disturbance and thought disorder in patients with a pre-existing psychotic disorder.

Induction of a Manic Episode in Patients with Bipolar Disease – CNS stimulants may induce a manic or mixed episode in patients. Prior to initiating treatment, screen patients for risk factors for developing a manic episode (e.g., comorbid or history of depressive symptoms or a family history of suicide, bipolar disorder, or depression).

New Psychotic or Manic Symptoms – CNS stimulants, at recommended doses, may cause psychotic or manic symptoms (e.g., hallucinations, delusional thinking, or mania) in patients without a prior history of psychotic illness or mania. In a pooled analysis of multiple short-term, placebo-controlled studies of CNS stimulants, psychotic or manic symptoms occurred in approximately 0.1% of CNS stimulant-treated patients, compared with 0% of placebo-treated patients. If such symptoms occur, consideration discontinuing methylphenidate hydrochloride chewable tablets.

Seizures
There is some clinical evidence that stimulants may lower the convulsive threshold in patients with prior history of seizures, in patients with prior EEG abnormalities in absence of seizures, and, very rarely, in patients without a history of seizures and no prior EEG evidence of seizures. In the presence of seizures, the drug should be discontinued.

Priapism
Prolonged and painful erections, sometimes requiring surgical intervention, have been reported with methylphenidate products in both pediatric and adult patients. Priapism was not reported with drug initiation but developed after some time on the drug, often subsequent to an increase in dose. Priapism has also appeared during a period of drug withdrawal (drug holidays or discontinuation): Patients who develop abnormally sustained or frequent and painful erections should seek immediate medical attention.

Peripheral Vasculopathy, Including Raynaud’s Phenomenon
Stimulants, including methylphenidate hydrochloride chewable tablets, used to treat ADHD are associated with peripheral vasculopathy, including Raynaud’s phenomenon. Signs and symptoms are usually intermittent and mild; however, very rare sequelae include digital ulceration and/or soft tissue breakdown. Effects of peripheral vasculopathy, including Raynaud’s phenomenon, were observed in postmarketing reports at different times and at therapeutic doses in all age groups throughout the course of treatment. Signs and symptoms generally improve after reduction in dose or discontinuation of drug. Careful observation for digital changes is necessary during treatment with ADHD stimulants. Further clinical evaluation (e.g., rheumatology referral) may be appropriate for certain patients.

Long-Term Suppression of Growth in Pediatric Patients
CNS stimulants have been associated with weight loss and slowing of growth rate in pediatric patients.

Careful follow-up of weight and height in pediatric patients ages 7 to 10 years who were randomized to either methylphenidate or non-medication treatment groups over 14 months, as well as in naturalistic subgroups of newly methylphenidate-treated and non-medication treated pediatric patients over 36 months (to the ages of 10 to 13 years), suggests that pediatric patients who received methylphenidate for 7 days per week throughout the year had a temporary slowing in growth rate (on average, a total of about 2 cm less growth in height and 2.7 kg less growth in weight over 3 years), without evidence of growth rebound during this development period.

Closely monitor growth (weight and height) in methylphenidate hydrochloride chewable tablets-treated pediatric patients. Pediatric patients who are not growing or gaining height or weight as expected may need to have their treatment interrupted (see PRECAUTIONS, PEDIATRIC USE).

Acute Angle Closure Glaucoma
There have been reports of angle closure glaucoma associated with methylphenidate treatment.

Although the mechanism is not clear, methylphenidate hydrochloride chewable tablets-treated patients considered at risk for acute angle closure glaucoma (e.g., patients with significant hyperopia) should be evaluated by an ophthalmologist.

Increased Intraocular Pressure and Glaucoma
There have been reports of an elevation of intraocular pressure (IOP) associated with methylphenidate treatment (see Adverse Reactions).

Prescribe methylphenidate hydrochloride chewable tablets to patients with open-angle glaucoma or abnormally increased IOP only if the benefit of treatment is considered to outweigh the risk. Closely monitor methylphenidate hydrochloride chewable tablets-treated patients with a history of abnormally increased IOP or open angle glaucoma.

Motor and Verbal Tics, and Worsening of Tourette’s Syndrome
CNS stimulants, including methylphenidate, have been associated with the onset or exacerbation of motor and verbal tics. Worsening of Tourette’s syndrome has also been reported. Assess the family history and clinically evaluate patients for tics or Tourette’s syndrome before initiating methylphenidate hydrochloride chewable tablets. Regularly monitor patients for the emergence or worsening of tics or Tourette’s syndrome with methylphenidate hydrochloride chewable tablets, and discontinue treatment if clinically appropriate.

USE IN CHILDREN LESS THAN SIX YEARS OF AGE
Methylphenidate hydrochloride chewable tablets should not be used in children under six years, since safety and efficacy in this age group have not been established.

DRUG ABUSE AND DEPENDENCE

Controlled Substance
Methylphenidate hydrochloride chewable tablets contains methylphenidate, a Schedule II controlled substance.

Abuse
Methylphenidate hydrochloride chewable tablets has a high potential for abuse and misuse which can lead to the development of a substance use disorder, including addiction (see Warnings and Precautions). Methylphenidate hydrochloride chewable tablets can be diverted for non-medical use into illicit channels or distribution.

Abuse is the intentional non-therapeutic use of a drug, even once, to achieve a desired psychological or physiological effect. Misuse is the intentional use, for therapeutic purposes, of a drug by an individual in a way other than prescribed by a health care provider or for whom it was not prescribed. Drug addiction is a cluster of behavioral, cognitive, and physiological phenomena that may include a strong desire to take the drug, difficulties in controlling drug use (e.g., continuing drug use despite harmful consequences, giving a higher priority to drug use than other activities and obligations), and possible tolerance or physical dependence.

Misuse and abuse of methylphenidate may cause increased heart rate, respiratory rate, or blood pressure; sweating; dilated pupils; hyperactivity; restlessness; insomnia; decreased appetite; loss of coordination; tremors; flushed skin; vomiting; and/or abdominal pain. Anxiety, psychosis, hostility, aggression, and suicidal or homicidal ideation have also been observed with CNS stimulants abuse and/or misuse. Misuse and abuse of CNS stimulants, including methylphenidate hydrochloride chewable tablets, can result in overdose and death (see Overdosage), and this risk is increased with higher doses or unapproved methods of administration, such as snorting or injection.

Dependence
Physical Dependence
Methylphenidate hydrochloride chewable tablets may produce physical dependence. Physical dependence is a state that develops as a result of physiological adaptation in response to repeated drug use, manifested by withdrawal signs and symptoms after abrupt discontinuation or a significant dose reduction of a drug.

Withdrawal signs and symptoms after abrupt discontinuation or dose reduction following prolonged use of CNS stimulants including methylphenidate hydrochloride chewable tablets include dysphoric mood; depression; fatigue; vivid, unpleasant dreams; insomnia or hypersomnia; increased appetite; and psychomotor retardation or agitation.

Tolerance
Methylphenidate hydrochloride chewable tablets may produce tolerance. Tolerance is a physiological state characterized by a reduced response to a drug after repeated administration (i.e., a higher dose of a drug is required to produce the same effect that was once obtained at a lower dose).

PRECAUTIONS

General
Patients with an element of agitation may react adversely; discontinue therapy if necessary.

Periodic CBC, differential, and platelet counts are advised during prolonged therapy.

Drug treatment is not indicated in all cases of this behavioral syndrome and should be considered only in light of the complete history and evaluation of the child. The decision to prescribe methylphenidate hydrochloride chewable tablets should depend on the physician’s assessment of the chronicity and severity of the child’s symptoms and their appropriateness for his/her age. Prescription should not depend solely on the presence of one or more of the behavioral characteristics.

When these symptoms are associated with acute stress reactions, treatment with methylphenidate hydrochloride chewable tablets are usually not indicated.

Long-term effects of methylphenidate hydrochloride chewable tablets in children have not been well established.

Information for Patients
Advise the patient to read the FDA-approved patient labeling (Medication Guide).

Abuse, Misuse, and Addiction
Educate patients and their families about the risks of abuse, misuse, and addiction of methylphenidate hydrochloride chewable tablets, which can lead to overdose and death, and proper disposal of any unused drug (see WARNINGS and PRECAUTIONS, DRUG ABUSE AND DEPENDENCE, OVERDOSAGE). Advise patients to store methylphenidate hydrochloride chewable tablets in a safe place, preferably locked, and instruct patients to not give methylphenidate hydrochloride chewable tablets to anyone else.

Risks to Patients with Serious Cardiac Disease
Advise patients that there are potential risks to patients with serious cardiac disease, including sudden death, with methylphenidate hydrochloride chewable tablets use. Instruct patients to contact a healthcare provider immediately if they develop symptoms such as exertional chest pain, unexplained syncope, or other symptoms suggestive of cardiac disease (see WARNINGS).

Increased Blood Pressure and Heart Rate
Advise patients that methylphenidate hydrochloride chewable tablets can elevate blood pressure and heart rate (see WARNINGS).

Psychiatric Adverse Reactions
Advise patients that methylphenidate hydrochloride chewable tablets, at recommended doses, can cause psychotic or manic symptoms, even in patients without a prior history of psychotic symptoms or mania (see WARNINGS).

Priapism
Advise patients, caregivers, and family members of the possibility of painful or prolonged penile erections (priapism). Instruct the patient to seek immediate medical attention in the event of priapism.

Circulation Problems in Fingers and Toes [Peripheral Vasculopathy, Including Raynaud’s Phenomenon]

- Instruct patients beginning treatment with methylphenidate hydrochloride chewable tablets about the risk of peripheral vasculopathy, including Raynaud’s phenomenon, and associated signs and symptoms: fingers or toes may feel numb, cool, painful, and/or may change color from pale, to blue, to red.
- Instruct patients to report to their physician any new numbness, pain, skin color change, or sensitivity to temperature in fingers or toes.
- Instruct patients to call their physician immediately with any signs of unexplained wounds appearing on fingers or toes while taking methylphenidate hydrochloride chewable tablets.
- Further clinical evaluation (e.g., rheumatology referral) may be appropriate for certain patients.

Suppression of Growth in Pediatric Patients
Advise patients, caregivers, and family members that methylphenidate hydrochloride chewable tablets can cause slowing of growth and weight loss (see Warnings).

Increased Intraocular Pressure and Glaucoma
Advise patients that IOP and glaucoma may occur during treatment with methylphenidate hydrochloride chewable tablets (see Warnings).

Motor and Verbal Tics, and Worsening of Tourette’s Syndrome
Advise patients that motor and verbal tics and worsening of Tourette’s Syndrome may occur during treatment with methylphenidate hydrochloride chewable tablets. Instruct the patients to notify their healthcare provider if emergence or worsening of tics or Tourette’s syndrome occurs (see WARNINGS).

Choking – Taking this product without adequate fluid may cause it to swell and block your throat or esophagus and may cause choking. Do not take this product if you have difficulty in swallowing. If you experience chest pain, vomiting, or difficulty in swallowing or breathing after taking this product, seek immediate medical attention.

Directions – Take this product (child or adult dose) with at least 8 ounces (a full glass) of water or other fluid. Taking this product without enough liquid may cause choking. See choking warning.

Phenylketonurics – Phenylalanine is a component of aspartame. Each 2.5 mg methylphenidate hydrochloride chewable tablet contains 0.35 mg of phenylalanine; each 5 mg methylphenidate hydrochloride chewable tablet contains 0.70 mg of phenylalanine and each 10 mg methylphenidate hydrochloride chewable tablet contains 1.40 mg of phenylalanine.

Drug Interactions
Monoamine Oxidase Inhibitors (MAOI)
Concomitant use of MAOIs and CNS stimulants, including methylphenidate hydrochloride chewable tablets can cause hypertensive crisis. Potential outcomes include death, stroke, myocardial infarction, aortic dissection, ophthalmological complications, eclampsia, pulmonary edema, and renal failure (see CONTRAINDICATIONS). Concomitant use of methylphenidate hydrochloride chewable tablets with MAOIs or within 14 days after discontinuing MAOI treatment is contraindicated.

Antihypertensive Drugs
Methylphenidate hydrochloride chewable tablets may decrease the effectiveness of drugs used to treat hypertension. Monitor blood pressure and adjust the dosage of the antihypertensive drug as needed.

Risperidone
Combined use of methylphenidate with risperidone when there is a change, whether an increase or decrease, in dosage of either or both medications, may increase the risk of extrapyramidal symptoms (EPS). Monitor for signs of EPS.

Methylphenidate hydrochloride chewable tablets may decrease the hypotensive effect of guanethidine. Use cautiously with pressor agents.

Human pharmacologic studies have shown that methylphenidate hydrochloride chewable tablets may inhibit the metabolism of coumarin anticoagulants, anticonvulsants (phenobarbital, diphenylhydantoin, primidone), phenylbutazone, and tricyclic drugs (imipramine, clomipramine, desipramine). Downward dosage adjustments of these drugs may be required when given concomitantly with methylphenidate hydrochloride chewable tablets.

Carcinogenesis, Mutagenesis, Impairment of Fertility
In a lifetime carcinogenicity study carried out in B6C3F1 mice, methylphenidate caused an increase in hepatocellular adenomas and, in males only, an increase in hepatoblastomas, at a daily dose of approximately 60 mg/kg/day. This dose is approximately 30 times and 2.5 times the maximum recommended human dose on a mg/kg and mg/m^2 basis, respectively. Hepatoblastoma is a relatively rare rodent malignant tumor type. There was no increase in total malignant hepatic tumors. The mouse strain used is sensitive to the development of hepatic tumors, and the significance of these results to humans is unknown.

Methylphenidate did not cause any increase in tumors in a lifetime carcinogenicity study carried out in F344 rats; the highest dose used was approximately 45 mg/kg/day, which is approximately 22 times and 4 times the maximum recommended human dose on a mg/kg and mg/m^2 basis, respectively.

Methylphenidate was not mutagenic in the in vitro Ames reverse mutation assay or in the in vitro mouse lymphoma cell forward mutation assay. Sister chromatid exchanges and chromosome aberrations were increased, indicative of a weak clastogenic response, in an in vitro assay in cultured Chinese Hamster Ovary (CHO) cells. The genotoxic potential of methylphenidate has not been evaluated in an in vivo assay.

Usage in Pregnancy
Adequate animal reproduction studies to establish safe use of methylphenidate hydrochloride chewable tablet during pregnancy have not been conducted. However, in a recently conducted study, methylphenidate has been shown to have teratogenic effects in rabbits when given in doses of 200 mg/kg/day, which is approximately 167 times and 78 times the maximum recommended human dose on a mg/kg and a mg/m^2 basis, respectively. In rats, teratogenic effects were not seen when the drug was given in doses of 75 mg/kg/day, which is approximately 62.5 and 13.5 times the maximum recommended human dose on a mg/kg and a mg/m^2 basis, respectively. Therefore, until more information is available, methylphenidate should not be prescribed for women of childbearing age unless, in the opinion of the physician, the potential benefits outweigh the possible risks.

ADVERSE REACTIONS

Nervousness and insomnia are the most common adverse reactions but are usually controlled by reducing dosage and omitting the drug in the afternoon or evening. Other reactions include hypersensitivity (including skin rash, urticaria, fever, arthralgia, exfoliative dermatitis, erythema multiforme with histopathological findings of necrotizing vasculitis, and thrombocytopenic purpura); anorexia; nausea; dizziness; palpitations; headache; dyskinesia; drowsiness; blood pressure and pulse changes, both up and down; tachycardia; angina; cardiac arrhythmia; abdominal pain; weight loss during prolonged therapy; libido changes; and rhabdomyolysis increased intraocular pressure and glaucoma, motor and verbal tics. There have been rare reports of Tourette’s syndrome. Toxic psychosis has been reported. Although a definite causal relationship has not been established, the following have been reported in patients taking this drug: instances of abnormal liver function, ranging from transaminase elevation to severe hepatic injury; isolated cases of cerebral arteritis and/or occlusion; leukopenia and/or anemia; transient depressed mood; a few instances of scalp hair loss; serotonin syndrome in combination with serotonergic drugs. Very rare reports of neuroleptic malignant syndrome (NMS) have been received, and, in most of these, patients were concurrently receiving therapies associated with NMS. In a single report, a ten year old boy who had been taking methylphenidate for approximately 18 months experienced an NMS-like event within 45 minutes of ingesting his first dose of venlafaxine. It is uncertain whether this case represented a drug-drug interaction, a response to either drug alone, or some other cause.

In children, loss of appetite, abdominal pain, weight loss during prolonged therapy, insomnia, and tachycardia may occur more frequently; however, any of the other adverse reactions listed above may also occur.

OVERDOSAGE

Clinical Effects of Overdose
Overdose of CNS stimulants is characterized by the following sympathomimetic effects:

- Cardiovascular effects including tachyarrhythmias, and hypertension or hypotension. Vasospasm, myocardial infarction, or aortic dissection may precipitate sudden cardiac death. Takotsubo cardiomyopathy may develop.
- CNS effects including psychomotor agitation, confusion, and hallucinations. Serotonin syndrome, seizures, cerebral vascular accidents, and coma may occur.
- Life-threatening hyperthermia (temperatures greater than 104°F) and rhabdomyolysis may develop.

Overdose Management
Consider the possibility of multiple drug ingestion. Because methylphenidate has a large volume of distribution and is rapidly metabolized, dialysis is not useful. Consider contacting the Poison Help line (1-800-222-1222) or a medical toxicologist for additional overdose management recommendations.

DOSAGE AND ADMINISTRATION

Prior to treating patients with Methylphenidate hydrochloride chewable tablets assess:

- for the presence of cardiac disease (i.e., perform a careful history, family history of sudden death or ventricular arrhythmia, and physical exam) (see WARNINGS).
- the family history and clinically evaluate patients for motor or verbal tics or Tourette’s syndrome (see WARNINGS).

Dosage should be individualized according to the needs and responses of the patient.

Directions – Take this product (child or adult dose) with at least 8 ounces (a full glass) of water or other fluid. Taking this product without enough liquid may cause choking. See choking warning.

Adults
Administer in divided doses 2 or 3 times daily, preferably 30 to 45 minutes before meals. Average dosage is 20 to 30 mg daily. Some patients may require 40 to 60 mg daily. In others, 10 to 15 mg daily will be adequate. Patients who are unable to sleep if medication is taken late in the day should take the last dose before 6 p.m.

Children (6 years and over)
Methylphenidate hydrochloride chewable tablets should be initiated in small doses, with gradual weekly increments. Daily dosage above 60 mg is not recommended.

If paradoxical aggravation of symptoms or other adverse effects occur, reduce dosage, or, if necessary, discontinue methylphenidate hydrochloride chewable tablets. Methylphenidate hydrochloride chewable tablets should be periodically discontinued to assess the patient’s condition. If improvement is not observed after appropriate dosage adjustment over a one-month period, the drug should be discontinued.

Start with 5 mg twice daily (before breakfast and lunch) with gradual increments of 5 to 10 mg weekly.

Drug treatment should not and need not be indefinite and usually may be discontinued after puberty.

HOW SUPPLIED

Each methylphenidate hydrochloride chewable tablet 10 mg is available as a white to off-white flat round chewable tablets debossed with 'AT' on left side and '262' on the right side of the bisect line and other side plain.

NDC: 72162-1306-1: 100 Tablets in a BOTTLE

Protect from moisture. Dispense in tight container with child-resistant closure.
Store at 20° to 25°C (68° to 77°F) [see USP Controlled Room Temperature].

Repackaged/Relabeled by:
Bryant Ranch Prepack, Inc.
Burbank, CA 91504

MEDICATION GUIDE Methylphenidate HCl Chewable Tablet, CII (meth'' il fen' i date hye'' droe klor' ide)

Read the Medication Guide that comes with methylphenidate hydrochloride chewable tablets before you or your child starts taking it and each time you get a refill. There may be new information. This Medication Guide does not take the place of talking to your healthcare provider about your or your child’s treatment with methylphenidate hydrochloride chewable tablets.

What is the most important information I should know about methylphenidate hydrochloride chewable tablets?

Methylphenidate hydrochloride chewable tablets may cause serious side effects, including:

- Abuse, misuse, and addiction. Methylphenidate hydrochloride chewable tablets have a high chance for abuse and misuse and may lead to substance use problems, including addiction. Misuse and abuse of methylphenidate hydrochloride chewable tablets, other methylphenidate containing medicines, and amphetamine containing medicines, can lead to overdose and death. The risk of overdose and death is increased with higher doses of methylphenidate hydrochloride chewable tablets or when it is used in ways that are not approved, such as snorting or injection.

- Heart-related problems:

- Mental (Psychiatric) problems:

- Circulation problems in fingers and toes [Peripheral vasculopathy, including Raynaud’s phenomenon]: fingers or toes may feel numb, cool, painful, and/or may change color from pale, to blue, to red.

What Are methylphenidate hydrochloride chewable tablets?
Methylphenidate hydrochloride chewable tablets are a central nervous system stimulant prescription medicine. Methylphenidate hydrochloride chewable tablets are tablets that are made to be chewed and swallowed. They are used for the treatment of Attention Deficit and Hyperactivity Disorder (ADHD). Methylphenidate hydrochloride chewable tablets may help increase attention and decrease impulsiveness and hyperactivity in patients with ADHD.

Methylphenidate hydrochloride chewable tablets should be used as a part of a total treatment program for ADHD that may include counseling or other therapies.

Methylphenidate hydrochloride chewable tablets are also used in the treatment of a sleep disorder called narcolepsy.

Methylphenidate hydrochloride chewable tablets are a federally controlled substance (CII) because it contains methylphenidate that can be a target for people who abuse prescription medicines or street drugs. Keep methylphenidate hydrochloride chewable tablets in a safe place to protect it from theft. Never give your methylphenidate hydrochloride chewable tablets to anyone else, because it may cause death or harm them. Selling or giving away methylphenidate hydrochloride chewable tablets may harm others, and is against the law.

Who should not take methylphenidate hydrochloride chewable tablets?
Methylphenidate hydrochloride chewable tablets should not be taken if you or your child:

- are very anxious, tense, or agitated
- have eye problems, including increased pressure in your eye, glaucoma, or problems with your close-up vision (farsightedness)
- have or had repeated movements or sounds (tics) or Tourette’s syndrome, or have a family history of tics or Tourette’s syndrome
- are taking or have taken within the past 14 days an antidepression medicine called a monoamine oxidase inhibitor or MAOI.
- are allergic to anything in methylphenidate hydrochloride chewable tablets. See the end of this Medication Guide for a complete list of ingredients.

Methylphenidate hydrochloride chewable tablets should not be used in children less than 6 years old because they have not been studied in this age group.

Methylphenidate hydrochloride chewable tablets may not be right for you or your child. Before starting methylphenidate hydrochloride chewable tablets tell your or your child’s healthcare provider about all health conditions (or a family history of) including:

- have heart problems, heart disease, heart defects, or high blood pressure
- mental problems including psychosis, mania, bipolar illness, or depression
- tics or Tourette’s syndrome
- seizures or have had an abnormal brain wave test (EEG)
- circulation problems in fingers and toes

Tell your healthcare provider if you or your child is pregnant, planning to become pregnant, or breastfeeding.

Can methylphenidate hydrochloride chewable tablets be taken with other medicines?

Tell your healthcare provider about all of the medicines that you or your child take including prescription and nonprescription medicines, vitamins, and herbal supplements.

Methylphenidate hydrochloride chewable tablets and some medicines may interact with each other and cause serious side effects. Sometimes the doses of other medicines will need to be adjusted while taking methylphenidate hydrochloride chewable tablets.

Your healthcare provider will decide whether methylphenidate hydrochloride chewable tablets can be taken with other medicines.

Especially tell your healthcare provider if you or your child takes:

- antidepression medicines including MAOIs
- seizure medicines
- blood thinner medicines
- blood pressure medicines
- cold or allergy medicines that contain decongestants

Know the medicines that you or your child takes. Keep a list of your medicines with you to show your healthcare provider and pharmacist.

Do not start any new medicine while taking methylphenidate hydrochloride chewable tablets without talking to your healthcare provider first.

How should methylphenidate hydrochloride chewable tablets be taken?

- Take methylphenidate hydrochloride chewable tablets exactly as prescribed. Your healthcare provider may adjust the dose until it is right for you or your child.
- Methylphenidate hydrochloride chewable tablets are usually taken 2 to 3 times a day.
- Take methylphenidate hydrochloride chewable tablets 30 to 45 minutes before a meal.

- Chew methylphenidate hydrochloride chewable tablets well and swallow with at least 8 ounces (a full glass) of water or other liquid. Methylphenidate hydrochloride chewable tablets can swell and cause choking if enough liquid is not taken with them. Get emergency medical care if you have chest pain, vomiting, or trouble swallowing, or breathing after taking a methylphenidate hydrochloride chewable tablet.

- From time to time, your healthcare provider may stop methylphenidate hydrochloride chewable tablets treatment for awhile to check ADHD symptoms.
- Your healthcare provider may do regular checks of the blood, heart, and blood pressure while you are taking methylphenidate hydrochloride chewable tablets. Children should have their height and weight checked often while taking methylphenidate hydrochloride chewable tablets. Methylphenidate hydrochloride chewable tablets treatment may be stopped if a problem is found during these check-ups.

If you or your child take too much methylphenidate hydrochloride chewable tablets, call your healthcare provider or Poison Helpline, at 1-800-222-1222 or go to the nearest hospital emergency room right away.

What are possible side effects of methylphenidate hydrochloride chewable tablets?

See “What is the most important information I should know about methylphenidate hydrochloride chewable tablets?” for information on reported heart and mental problems.
Other serious side effects include:

- Slowing of growth (height and weight) in children. Children should have their height and weight checked often during treatment with methylphenidate hydrochloride chewable tablets. Your healthcare provider may stop your child’s methylphenidate hydrochloride chewable tablets treatment if they are not growing or gaining weight as expected.
- Seizures, mainly in patients with a history of seizures
- Painful and prolonged erections (priapism) have occurred with methylphenidate. If you or your child develop priapism, seek medical help right away. Because of the potential for lasting damage, priapism should be evaluated by a healthcare provider immediately.
- Circulation problems in fingers and toes (peripheral vasculopathy, including Raynaud’s phenomenon): fingers or toes may feel numb, cool, painful, and/or may change color from pale, to blue, to red. Tell your healthcare provider if you have or your child has numbness, pain, skin color change, or sensitivity to temperature in your fingers or toes or if you have or your child has any signs of unexplained wounds appearing on fingers or toes while taking methylphenidate hydrochloride chewable tablets.
- Eyes problems (increased pressure in the eye and glaucoma). Call your healthcare provider right away if you or your child develop changes in your vision or eye pain, swelling, or redness.
- New or worsening tics or worsening Tourette’s syndrome. Tell your healthcare provider if you or your child get any new or worsening tics or worsening Tourette’s syndrome during treatment with methylphenidate hydrochloride chewable tablets.

Common side effects include:

Talk to your healthcare provider if you or your child has side effects that are bothersome or do not go away.

This is not a complete list of possible side effects. Ask your healthcare provider or pharmacist for more information.

Call your doctor for medical advice about side effects. You may report side effects to FDA at 1-800-FDA-1088.

How should I store methylphenidate hydrochloride chewable tablets?

- Store methylphenidate hydrochloride chewable tablets in a safe place at room temperature, at 20° to 25°C (68° to 77°F). [see USP Controlled Room Temperature]. Protect from moisture.
- Dispose of remaining, unused, or expired methylphenidate hydrochloride chewable tablets by a medicine take back program at a U.S. Drug Enforcement Administration (DEA) authorized collection site. If no takeback program or DEA authorized collector is available, mix methylphenidate hydrochloride chewable tablets with an undesirable, nontoxic substance such as dirt, cat litter, or used coffee grounds to make it less appealing to children and pets. Place the mixture in a container such as a sealed plastic bag and throw away methylphenidate hydrochloride chewable tablets in the household trash. Visit www.fda.gov/drugdisposal for additional information on disposal of unused medicines.
- Keep methylphenidate hydrochloride chewable tablets and all medicines out of the reach of children.

General information about methylphenidate hydrochloride chewable tablets
Medicines are sometimes prescribed for purposes other than those listed in a Medication Guide. Do not use methylphenidate hydrochloride chewable tablets for a condition for which it was not prescribed. Do not give methylphenidate hydrochloride chewable tablets to other people, even if they have the same condition. It may harm them and it is against the law.
This Medication Guide summarizes the most important information about methylphenidate hydrochloride chewable tablets. If you would like more information, talk with your healthcare provider. You can ask your healthcare provider or pharmacist for information about methylphenidate hydrochloride chewable tablets that is written for healthcare professionals. For more information, please contact Camber Pharmaceuticals, Inc. at 1-866-495-8330.

What are the ingredients in methylphenidate hydrochloride chewable tablets?

CAUTION PHENYLKETONURICS: Methylphenidate hydrochloride chewable tablets contain phenylalanine.

Active Ingredient: methylphenidate hydrochloride USP

Inactive Ingredients: aspartame, lactose anhydrous, microcrystalline cellulose, guar gum, grape flavor, pregelatinized starch, and stearic acid.

Medication Guide available at http://camberpharma.com/medication-guides

Manufactured by:
Ascent Pharmaceuticals, Inc.
Central Islip, NY 11722

Manufactured for:
Camber Pharmaceuticals, Inc.
Piscataway, NJ 08854

This Medication Guide has been approved by the U.S. Food and Drug Administration. Revised 09/2023

PACKAGE LABEL

Methylphenidate Hcl 10 mg (CII) Tab #100